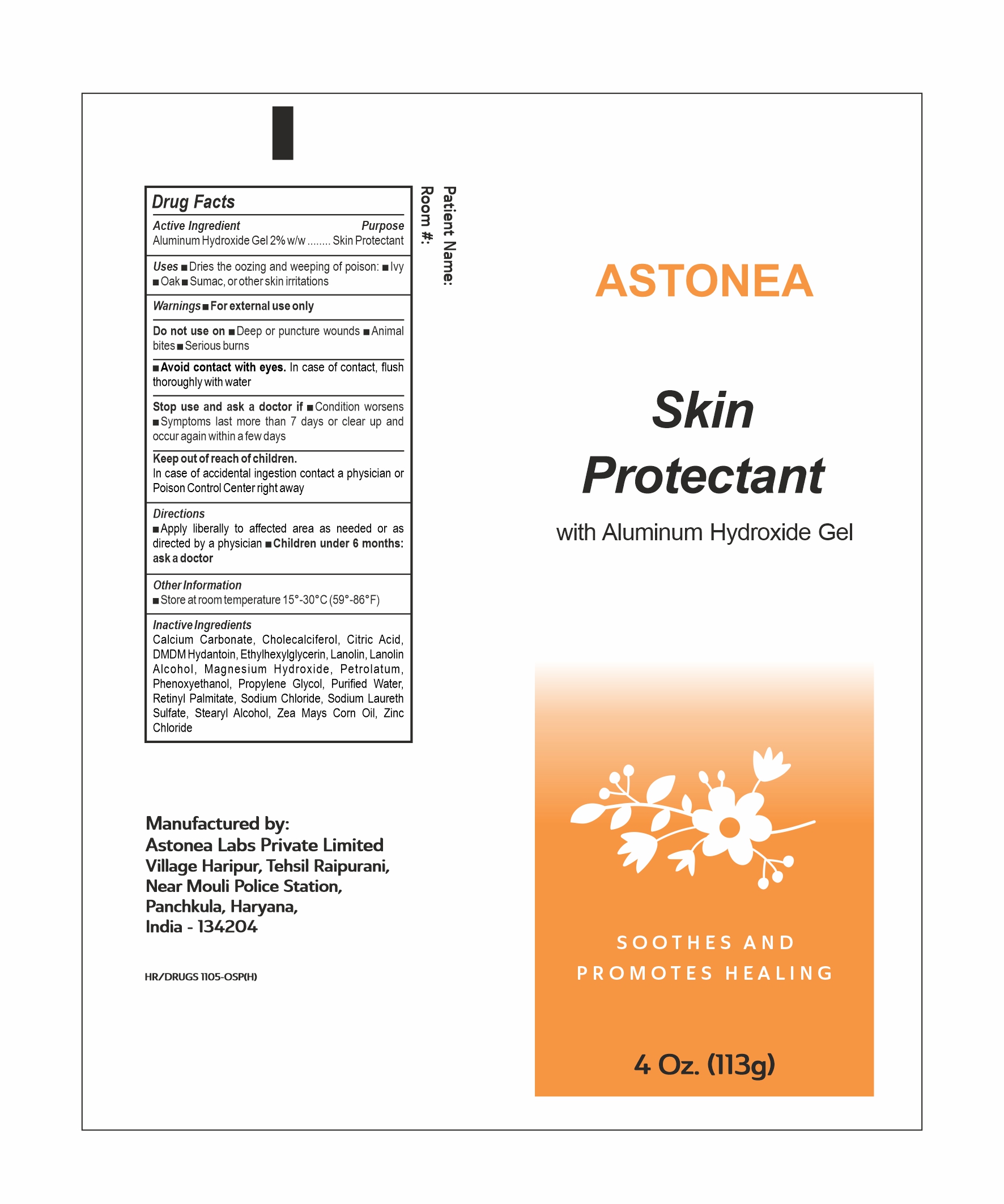 DRUG LABEL: ASTONEAGRAN
NDC: 77338-021 | Form: OINTMENT
Manufacturer: ASTONEA LABS PRIVATE LIMITED
Category: otc | Type: HUMAN OTC DRUG LABEL
Date: 20240625

ACTIVE INGREDIENTS: ALUMINUM HYDROXIDE 2 g/100 g
INACTIVE INGREDIENTS: CALCIUM CARBONATE; LANOLIN; ANHYDROUS CITRIC ACID; VITAMIN A PALMITATE; PETROLATUM; PROPYLENE GLYCOL; SODIUM CHLORIDE; SODIUM LAURETH SULFATE; STEARYL ALCOHOL; WATER; ZINC CHLORIDE; DMDM HYDANTOIN; CORN OIL; CHOLECALCIFEROL; ETHYLHEXYLGLYCERIN; MAGNESIUM HYDROXIDE; LANOLIN ALCOHOLS; PHENOXYETHANOL

ASTONEA Gran

Active Ingredients:

Aluminium Hydroxide Gel 2 % w/w

Purpose

Skin Protectant

Uses:

- Dries the oozing, and weeping of poison ivy, poison oak, or poison sumac, or other skin irritations

Warnings:

For external use only.

DO NOT USE

■Deep or puncture wounds ■Animal bites ■Serious burns

Avoid contact with eyes. In case of contact, ﬂush thoroughly with water

Stop use and ask a doctor if

■Condition worsens

■Symptoms last more than 7 days or clear up and occur again within a few days

Keep out of reach of children

In case of accidental ingestion contact a physician or Poison Control Center right away

Directions

Apply liberally to affected area as needed or as directed by a physician ■Children under 6 months: ask a doctor

Other Information

■Store at room temperature 15°-30°C (59°-86°F)

INACTIVE INGREDIENT

Calcium Carbonate, Cholecalciferol, Citric Acid, DMDM Hydantoin, Ethylhexylglycerin, Lanolin, Lanolin Alcohol, Magnesium Hydroxide, Petrolatum, Phenoxyethanol, Propylene Glycol, Puriﬁed Water, Retinyl Palmitate, Sodium Chloride, Sodium Laureth Sulfate, Stearyl Alcohol, Zea Mays Corn Oil, Zinc Chloride